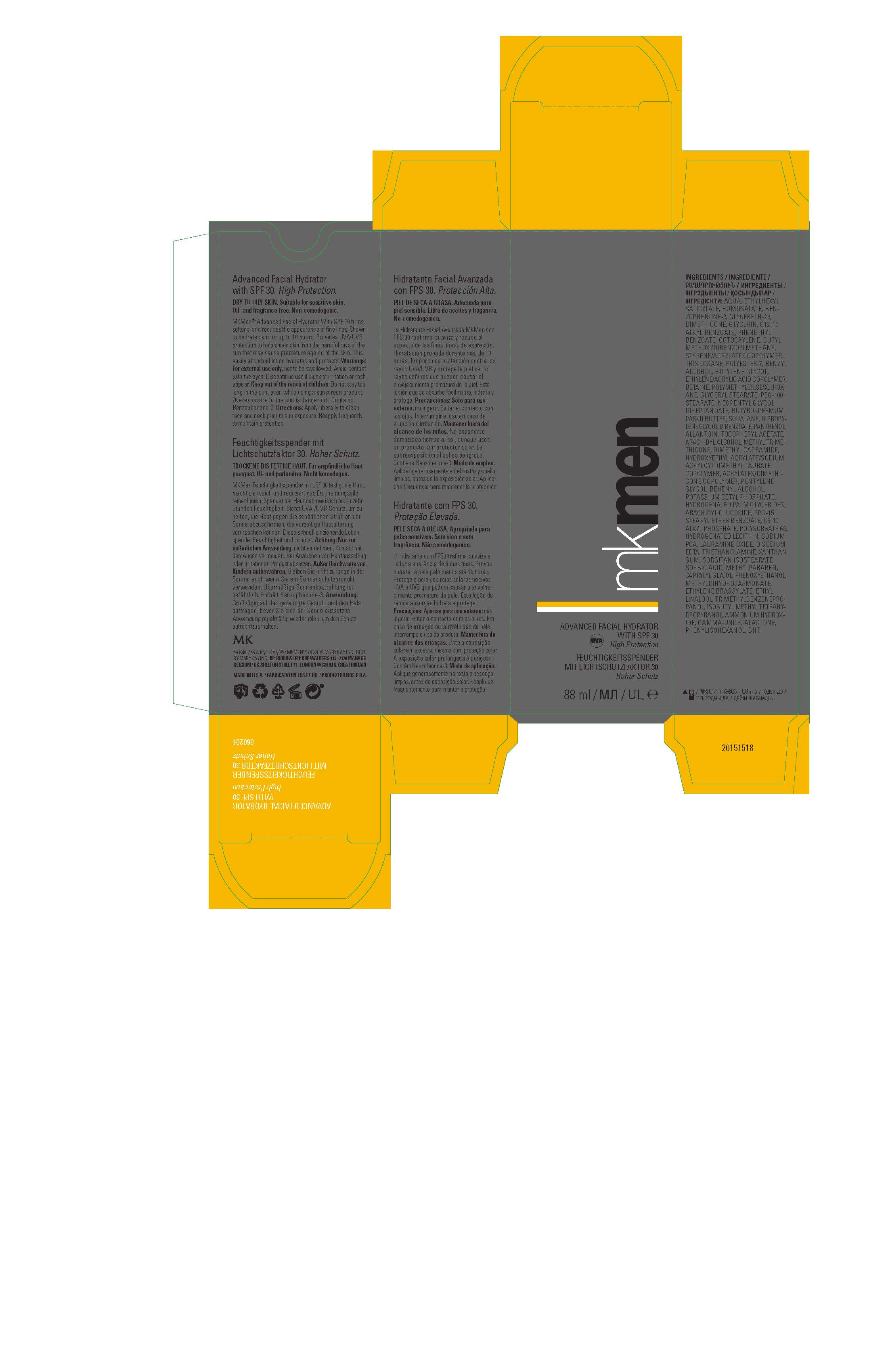 DRUG LABEL: MK Men Advanced Facial Hydrator Sunscreen SPF 30
NDC: 51531-0294 | Form: LOTION
Manufacturer: Mary Kay Inc.
Category: otc | Type: HUMAN OTC DRUG LABEL
Date: 20200824

ACTIVE INGREDIENTS: AVOBENZONE 2 g/100 mL; HOMOSALATE 5 g/100 mL; OCTOCRYLENE 2 g/100 mL; OCTISALATE 5 g/100 mL; OXYBENZONE 4 g/100 mL
INACTIVE INGREDIENTS: WATER; GLYCERETH-26; DIMETHICONE; GLYCERIN; ALKYL (C12-15) BENZOATE; PHENETHYL BENZOATE; TRISILOXANE; POLYESTER-7; BENZYL ALCOHOL; BETAINE; BUTYLENE GLYCOL; ACRYLIC ACID/ETHYLENE COPOLYMER (600 MPA.S); POLYMETHYLSILSESQUIOXANE (4.5 MICRONS); GLYCERYL MONOSTEARATE; NEOPENTYL GLYCOL DIHEPTANOATE; PHENOXYETHANOL; DIPROPYLENE GLYCOL DIBENZOATE; HYDROXYETHYL ACRYLATE/SODIUM ACRYLOYLDIMETHYL TAURATE COPOLYMER (45000 MPA.S AT 1%); PEG-100 STEARATE; CAPRYLYL GLYCOL; ARACHIDYL ALCOHOL; METHYL TRIMETHICONE; DIMETHYL CAPRAMIDE; SQUALANE; SHEA BUTTER; PENTYLENE GLYCOL; DOCOSANOL; POTASSIUM CETYL PHOSPHATE; XANTHAN GUM; LAURAMINE OXIDE; EDETATE DISODIUM; HYDROGENATED PALM GLYCERIDES; METHYLPARABEN; ARACHIDYL GLUCOSIDE; PPG-15 STEARYL ETHER BENZOATE; POLYSORBATE 60; HYDROGENATED SOYBEAN LECITHIN; PANTHENOL; .ALPHA.-TOCOPHEROL ACETATE; SORBIC ACID; ALLANTOIN; METHYL DIHYDROJASMONATE (SYNTHETIC); BUTYLATED HYDROXYTOLUENE; SODIUM PYRROLIDONE CARBOXYLATE; TROLAMINE; SORBITAN ISOSTEARATE; ETHYLENE BRASSYLATE; ETHYL LINALOOL; TRIMETHYLBENZENEPROPANOL; 2-ISOBUTYL-4-METHYLTETRAHYDROPYRAN-4-OL; AMMONIA; .GAMMA.-UNDECALACTONE; PHENYLISOHEXANOL

MK Men SPF 30 Sunscreen EU Export Only

Indications:

Shown to hydrate skin for up to 10 hours.

Provides UVA/UVB protection to help shield skin from the harmful rays of the sun that may cause premature ageing of the skin.

Warnings:

For external use only, not to be swallowed.

Avoid contact with the eyes.

Discontinue use if signs of irritation or rash appear.

Keep out of the reach of children.

Do not stay too long in the sun, even while using a sunscreen product.

Overexposure to the sun is dangerous.

Contains Benzophenone-3.

Directions:

Apply liberally to clean face and neck prior to sun exposure.

Reapply frequently to maintain protection.

OTHER INGEDIENTS:

AQUA, ETHYLHEXYL
SALICYLATE, HOMOSALATE, BENZOPHENONE-3, GLYCERETH-26,
DIMETHICONE, GLYCERIN, C12-15
ALKYL BENZOATE, PHENETHYL
BENZOATE, OCTOCRYLENE, BUTYL
METHOXYDIBENZOYLMETHANE,
STYRENE/ACRYLATES COPOLYMER,
TRISILOXANE, POLYESTER-7, BENZYL
ALCOHOL, BUTYLENE GLYCOL,
ETHYLENE/ACRYLIC ACID COPOLYMER,
BETAINE, POLYMETHYLSILSESQUIOXANE, GLYCERYL STEARATE, PEG-100
STEARATE, NEOPENTYL GLYCOL
DIHEPTANOATE, BUTYROSPERMUM
PARKII BUTTER, SQUALANE, DIPROPYLENE GLYCOL DIBENZOATE, PANTHENOL,
ALLANTOIN, TOCOPHERYL ACETATE,
ARACHIDYL ALCOHOL, METHYL TRIMETHICONE, DIMETHYL CAPRAMIDE,
HYDROXYETHYL ACRYLATE/SODIUM
ACRYLOYLDIMETHYL TAURATE
COPOLYMER, ACRYLATES/DIMETHICONE COPOLYMER, PENTYLENE
GLYCOL, BEHENYL ALCOHOL,
POTASSIUM CETYL PHOSPHATE,
HYDROGENATED PALM GLYCERIDES,
ARACHIDYL GLUCOSIDE, PPG-15
STEARYL ETHER BENZOATE, C9-15
ALKYL PHOSPHATE, POLYSORBATE 60,
HYDROGENATED LECITHIN, SODIUM
PCA, LAURAMINE OXIDE, DISODIUM
EDTA, TRIETHANOLAMINE, XANTHAN
GUM, SORBITAN ISOSTEARATE,
SORBIC ACID, METHYLPARABEN,
CAPRYLYL GLYCOL, PHENOXYETHANOL,
METHYLDIHYDROJASMONATE,
ETHYLENE BRASSYLATE, ETHYL
LINALOOL, TRIMETHYLBENZENEPROPANOL, ISOBUTYL METHYL TETRAHYDROPYRANOL, AMMONIUM HYDROXIDE, GAMMA-UNDECALACTONE,
PHENYLISOHEXANOL, BHT.

Principal Display Panel- 88 mL carton

MK Men

ADVANCED FACIAL HYDRATOR
WITH SPF 30
High Protection UVA

88 mL